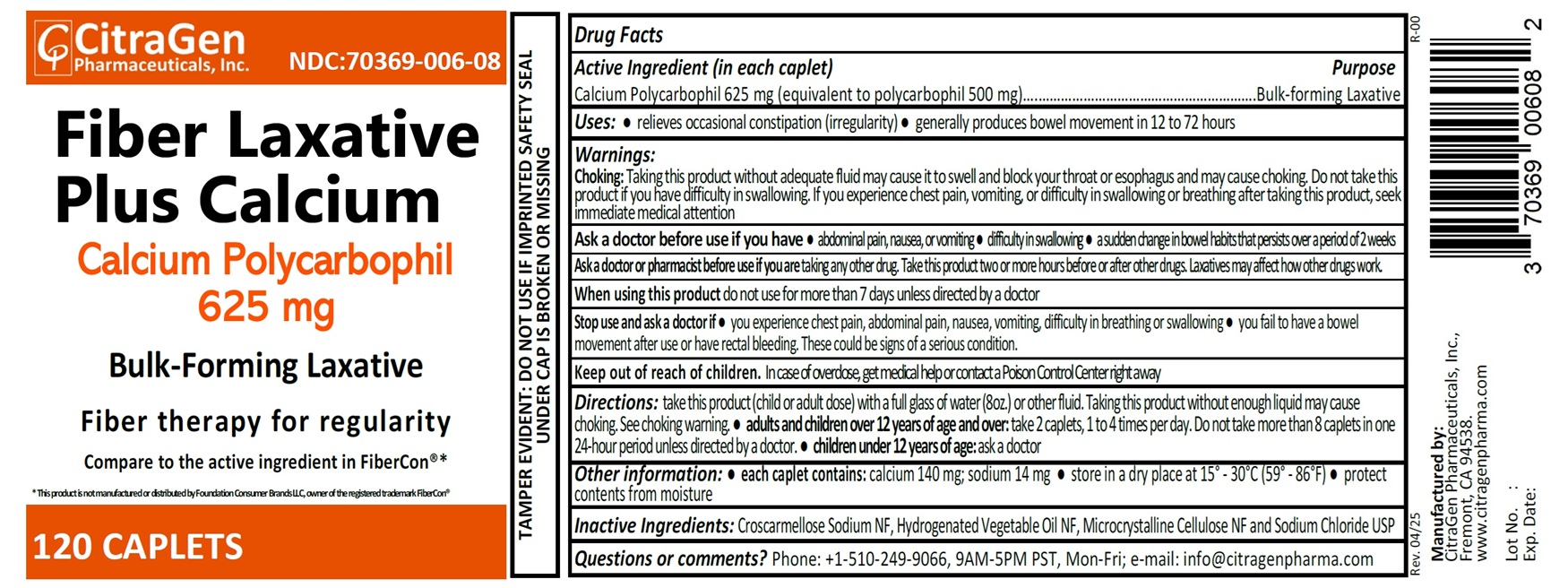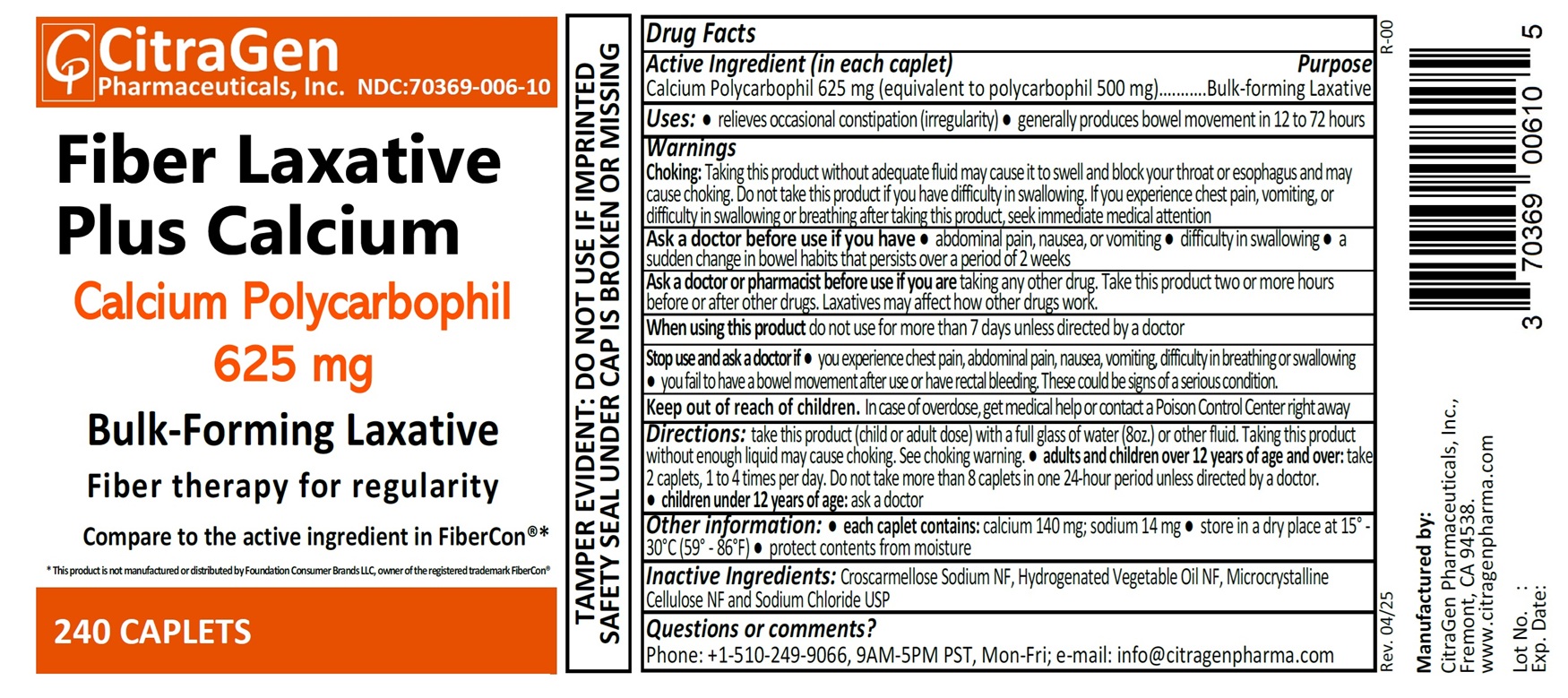 DRUG LABEL: Calcium Polycarbophil
NDC: 70369-006 | Form: TABLET
Manufacturer: CITRAGEN PHARMACEUTICALS, INC.
Category: otc | Type: HUMAN OTC DRUG LABEL
Date: 20250403

ACTIVE INGREDIENTS: CALCIUM POLYCARBOPHIL 625 mg/1 1
INACTIVE INGREDIENTS: CROSCARMELLOSE SODIUM; HYDROGENATED COTTONSEED OIL; MICROCRYSTALLINE CELLULOSE; SODIUM CHLORIDE

Fiber Laxative Plus Calcium (Calcium Polycarbophil 625 mg) Tablets

Drug Facts

Active Ingredient (in each caplet)

Calcium Polycarbophil 625 mg (equivalent to polycarbophil 500 mg)

Purpose

Bulk-forming Laxative

Uses

- relieves occasional constipation (irregularity)
- generally produces bowel movement in 12 to 72 hours

Warnings

Choking:

Taking this product without adequate fluid may cause it to swell and block your throat or esophagus and may cause choking.

Do not take this product if you have difficulty in swallowing. If you experience chest pain, vomiting, or difficulty in swallowing

or breathing after taking this product, seek immediate medical attention

Ask a doctor before use if you have

- abdominal pain, nausea, or vomiting
- difficulty in swallowing
- a sudden change in bowel habits that persists over a period of 2 weeks

Ask a doctor or pharmacist before use if you are

- taking any other drug.
- Take this product two or more hours before or after other drugs.
- Laxatives may affect how other drugs work.

When using this product

- do not use for more than 7 days unless directed by a doctor

Stop use and ask a doctor if

- you experience chest pain, abdominal pain, nausea, vomiting, difficulty in breathing or swallowing
- you fail to have a bowel movement after use or have rectal bleeding. These could be signs of a serious condition.

OVERDOSAGE

In case of overdose, get medical help or contact a Poison Control Center right away

Directions

- take this product (child or adult dose) with a full glass of water (8oz.) or other fluid. Taking this product without enough liquid may cause choking. See choking warning
- adults and children over 12 years of age and over: take 2 caplets, 1 to 4 times per day. Do not take more than 8 caplets in one 24-hour period unless directed by a doctor.
- children under 12 years of age: ask a doctor

Other information

- each caplet contains: calcium 140 mg; sodium 14 mg
- store in a dry place at 15° - 30°C (59° - 86°F)
- protect contents from moisture

Inactive Ingredients

Croscarmellose Sodium NF, Hydrogenated Vegetable Oil NF, Microcrystalline Cellulose NF and Sodium Chloride USP

Questions or comments?

Phone: +1-510-249-9066, 9AM-5PM PST, Mon-Fri; e-mail: info@citragenpharma.com

TAMPER EVIDENT: DO NOT USE IF IMPRINTED SAFETY SEAL UNDER CAP IS BROKEN OR MISSING

Manufactured by:

CitraGen Pharmaceuticals, Inc.,
Fremont, CA 94538.

www.citragenpharma.com

Rev. 04/25 R-00

PACKAGE LABEL

CitraGen Pharmaceuticals, Inc.

NDC: 70369-006-08

Calcium Polycarbophil Tablets 625 mg

Fiber Laxative Plus Calcium

Calcium Polycarbophil 625 mg

Bulk-Forming Laxative

Fiber Therapy for regularity

Compare to the active ingredient in FiberCon® [This product is not manufactured or distributed by Foundation Consumer Brands LLC, owner of the registered trademark FiberCon®]

120 Caplets

PACKAGE LABEL

CitraGen Pharmaceuticals, Inc.

NDC: 70369-006-10

Calcium Polycarbophil Tablets 625 mg

Fiber Laxative Plus Calcium

Calcium Polycarbophil 625 mg

Bulk-Forming Laxative

Fiber Therapy for regularity

Compare to the active ingredient in FiberCon® [This product is not manufactured or distributed by Foundation Consumer Brands LLC, owner of the registered trademark FiberCon®]

240 Caplets